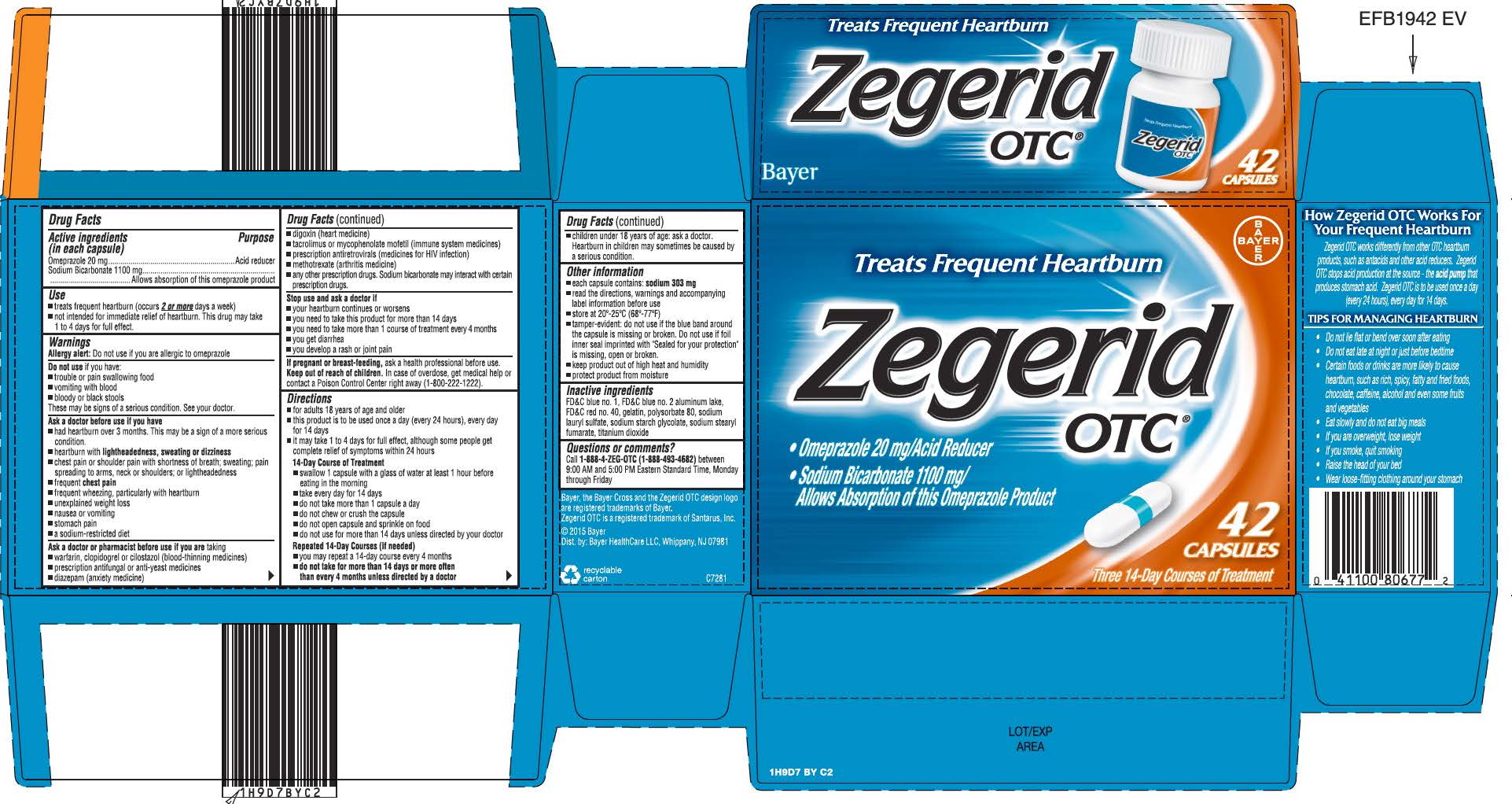 DRUG LABEL: Zegerid OTC
NDC: 11523-7276 | Form: CAPSULE, GELATIN COATED
Manufacturer: Bayer HealthCare LLC.
Category: otc | Type: HUMAN OTC DRUG LABEL
Date: 20241206

ACTIVE INGREDIENTS: OMEPRAZOLE 20 mg/1 1; SODIUM BICARBONATE 1100 mg/1 1
INACTIVE INGREDIENTS: SODIUM STEARYL FUMARATE; FD&C RED NO. 40; FD&C BLUE NO. 1; POLYSORBATE 80; SODIUM LAURYL SULFATE; FD&C BLUE NO. 2; TITANIUM DIOXIDE

Zegerid OTC

Drug Facts

Active ingredients (in each capsule)

Omeprazole 20 mg

Sodium Bicarbonate 1100 mg

Purpose

Acid reducer

Allows absorption of this omeprazole product

Use

● treats frequent heartburn (occurs 2 or more days a week)

● not intended for immediate relief of heartburn. This drug may take 1 to 4 days for full effect.

Warnings

Allergy alert: Do not use if you are allergic to omeprazole

Do not use if you have:

● trouble or pain swallowing food

● vomiting with blood

● bloody or black stools

These may be signs of a serious condition. See your doctor.

Ask a doctor before use if you have

● had heartburn over 3 months. This may be a sign of a more serious condition.

● heartburn with lightheadedness, sweating or dizziness

● chest pain or shoulder pain with shortness of breath; sweating; pain spreading to arms, neck or shoulders; or lightheadedness

● frequent chest pain

● frequent wheezing, particularly with heartburn

● unexplained weight loss

● nausea or vomiting

● stomach pain

● a sodium-restricted diet

Ask a doctor or pharmacist before use if you are taking

● warfarin, clopidogrel or cilostazol (blood-thinning medicines)

● prescription antifungal or anti-yeast medicines

● diazepam (anxiety medicine)

● digoxin (heart medicine)

● tacrolimus or mycophenolate mofetil (immune system medicines)

● prescription antiretrovirals (medicines for HIV infection)

● methotrexate (arthritis medicine)

● any other prescription drugs. Sodium bicarbonate may interact

with certain prescription drugs.

Stop use and ask a doctor if

● your heartburn continues or worsens

● you need to take this product for more than 14 days

● you need to take more than 1 course of treatment every 4 months

● you get diarrhea

● you develop a rash or joint pain

PREGNANCY OR BREAST FEEDING

If pregnant or breast-feeding, ask a health professional before use

Keep out of reach of children. In case of overdose, get medical help or contact a Poison Control Center right away (1-800-1222).

Directions

● for adults 18 years of age and older

● this product is to be used once a day (every 24 hours), every

day for 14 days

● it may take 1 to 4 days for full effect, although some people

get complete relief of symptoms within 24 hours

14-Day Course of Treatment

● swallow 1 capsule with a glass of water at least 1 hour

before eating in the morning

● take every day for 14 days

● do not take more than 1 capsule a day

● do not chew or crush the capsule

● do not open capsule and sprinkle on food

● do not use for more than 14 days unless directed by your

doctor

Repeated 14-Day Courses (if needed)

● you may repeat a 14-day course every 4 months

● do not take for more than 14 days or more often than

every 4 months unless directed by a doctor

● children under 18 years of age: ask a doctor.

Heartburn in children may sometimes be caused by a

serious condition.

Other information

● each tablet contains: sodium 303 mg

● read the directions, warnings and accompanying label

information before use

● store at 20°-25°C (68°-77°F)

● tamper-evident: do not use if the blue band around the

capsule is missing or broken. Do not use if foil inner seal

imprinted with “Sealed for your protection” is missing, open or

broken.

● keep product out of high heat and humidity

● protect product from moisture

Inactive ingredients

FD&C blue No. 1, FD&C blue No. 2 aluminum lake, FD&C red No. 40, gelatin, polysorbate 80, sodium lauryl sulfate, sodium starch glycolate, sodium stearyl fumarate, titanium dioxide

Questions or comments

Call 1-888-4-ZEG-OTC (1-888-493-4682) between 9:00 AM and 5:00 PM Eastern Standard Time, Monday through Friday

42 count carton

Treats Frequent Heartburn

Zegerid OTC ®

• Omeprazole 20 mg/Acid Reducer
• Sodium Bicarbonate 1100 mg/
Allows Absorption of this Omeprazole Product

42 CAPSULES

Three 14-Day Courses of Treatment